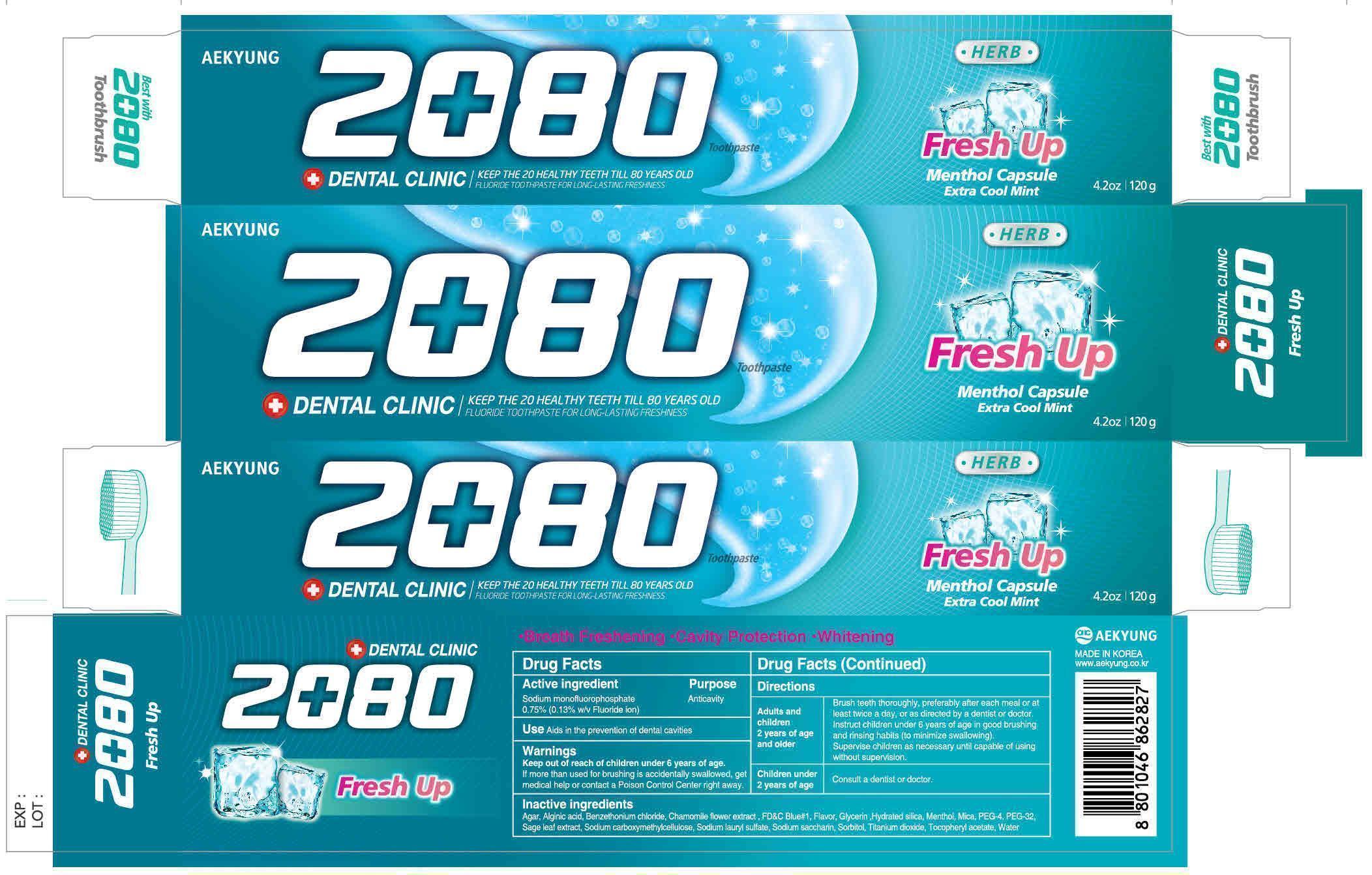 DRUG LABEL: Dental Clinic 2080 Fresh Up
NDC: 67225-0005 | Form: PASTE
Manufacturer: Aekyung Industrial Co., Ltd.
Category: otc | Type: HUMAN OTC DRUG LABEL
Date: 20160714

ACTIVE INGREDIENTS: SODIUM MONOFLUOROPHOSPHATE 0.156 g/120 g
INACTIVE INGREDIENTS: SORBITOL 72 g/120 g; SODIUM LAURYL SULFATE 3.12 g/120 g; CARBOXYMETHYLCELLULOSE SODIUM 0.6 g/120 g; SACCHARIN SODIUM 0.156 g/120 g; ALPHA-TOCOPHEROL ACETATE 0.12 g/120 g; HYDRATED SILICA 22.8 g/120 g; WATER 12.07 g/120 g; MENTHOL 0.6 g/120 g; CHAMOMILE FLOWER OIL 0.006 g/120 g; FD&C BLUE NO. 1 0.00156 g/120 g

WARNINGS

If more than used for brushing is accidentally swallowed, get medical help or contact a Poison Control Center right away

Keep out of reach of children under 6 years of age

ACTIVE INGREDIENT

Sodium monofluorophosphate 0.75% (0.13% w/v Fluoride ion)

INACTIVE INGREDIENT

Sodium carboxymethylcellulose, Sodium lauryl sulfate, Sodium saccharin, Sorbitol, Titanium dioxide, Tocopheryl acetate, Water, Hydrated Silica, Menthol, PEG-4, PEG-32, Flavor, Glycerin, Mica, Sage leaf extract, Agar, Alginic acid, Benzethonium chloride, Chamomille flower extract, FD&C Blue No 1

Purpose Anticavity

DOSAGE AND ADMINISTRATION

Adults and children 2 years of age and older

Brush teeth thoroughly, preferably after each meal or at least twice a day or as directed by a dentist or doctor.

Instruct children under 6 years of age in good brushing ad rinsing habits (to minimize swallowing).

Supervise children as necessary until capable of using without supervision.

Children under 2 years of age

Consult a dentist or doctor

INDICATIONS AND USAGE

Aids in the prevention of dental cavities